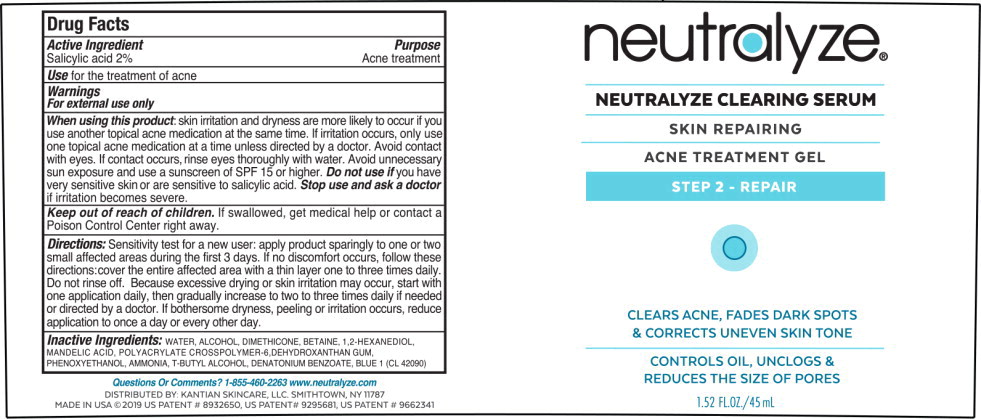 DRUG LABEL: Neutralyze Clearing Serum
NDC: 57524-015 | Form: GEL
Manufacturer: Kantian Skincare, LLC
Category: otc | Type: HUMAN OTC DRUG LABEL
Date: 20241004

ACTIVE INGREDIENTS: Salicylic Acid 20 mg/1 mL
INACTIVE INGREDIENTS: Water; Alcohol; Dimethicone; Betaine; 1,2-hexanediol; Mandelic Acid; Ammonium Acryloyldimethyltaurate, dimethylacrylamide, lauryl methacrylate and laureth-4 methacrylate copolymer, trimethylolpropane triacrylate crosslinked (45000 mpa.s); Dehydroxanthan Gum; Phenoxyethanol; Ammonia; Tert-Butyl Alcohol; Denatonium Benzoate; FD&C Blue No. 1

Drug Facts

Active Ingredient

Salicylic acid 2%

Purpose

Acne treatment

Use

for the treatment of acne

Warnings

For external use only

When using this product: skin irritation and dryness are more likely to occur if you use another topical acne medication at the same time. If irritation occurs, only use one topical acne medication at a time unless directed by a doctor. Avoid contact with eyes. If contact occurs, rinse eyes thoroughly with water. Avoid unnecessary sun exposure and use a sunscreen of SPF15 or higher.

Do not use if you have very sensitive skin or are sensitive to salicylic acid.

Stop use and ask a doctor if irritation becomes severe.

Keep out of reach of children. If swallowed, get medical help or contact a Poison Control Center right away.

Directions:

Sensitivity test for a new user: apply product sparingly to one or two small affected areas during the first 3 days. If no discomfort occurs, follow these directions: cover the entire affected area with a thin layer one to three times daily. Do not rinse off. Because excessive drying or skin irritation may occur, start with one application daily, then gradually increase to two to three times daily if needed or directed by a doctor. If bothersome dryness, peeling or irritation occurs, reduce application to once a day or every other day.

Inactive Ingredients:

WATER, ALCOHOL, DIMETHICONE, BETAINE, 1,2-HEXANEDIOL, MANDELIC ACID, POLYACRYLATE CROSSROLYMER-6,DEHYDROXANTHAN GUM, PHENOXYETHANOL, AMMONIA, T-BUTYL ALCOHOL, DENATONIUM BENZOATE, BLUE 1 (CL 42090)

Principal Display Panel – Bottle Label.

neutralyze®

NEUTRALYZE CLEARING SERUM

SKIN REPAIRING

ACNE TREATMENT GEL

STEP 2 – REPAIR

CLEARS ACNE, FADES DARK SPOTS
& CORRECTS UNEVEN SKIN TONE

CONTROLS OIL, UNCLOGS &
REDUCES THE SIZE OF PORES

1.52 FL. OZ./45 mL